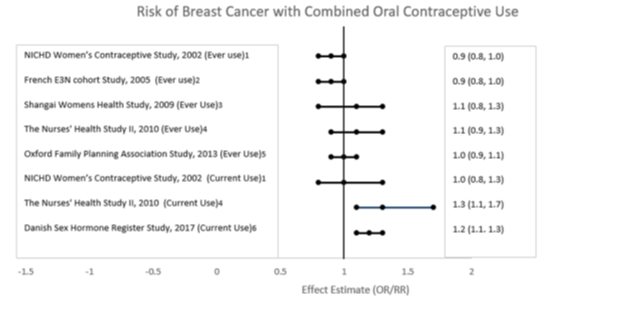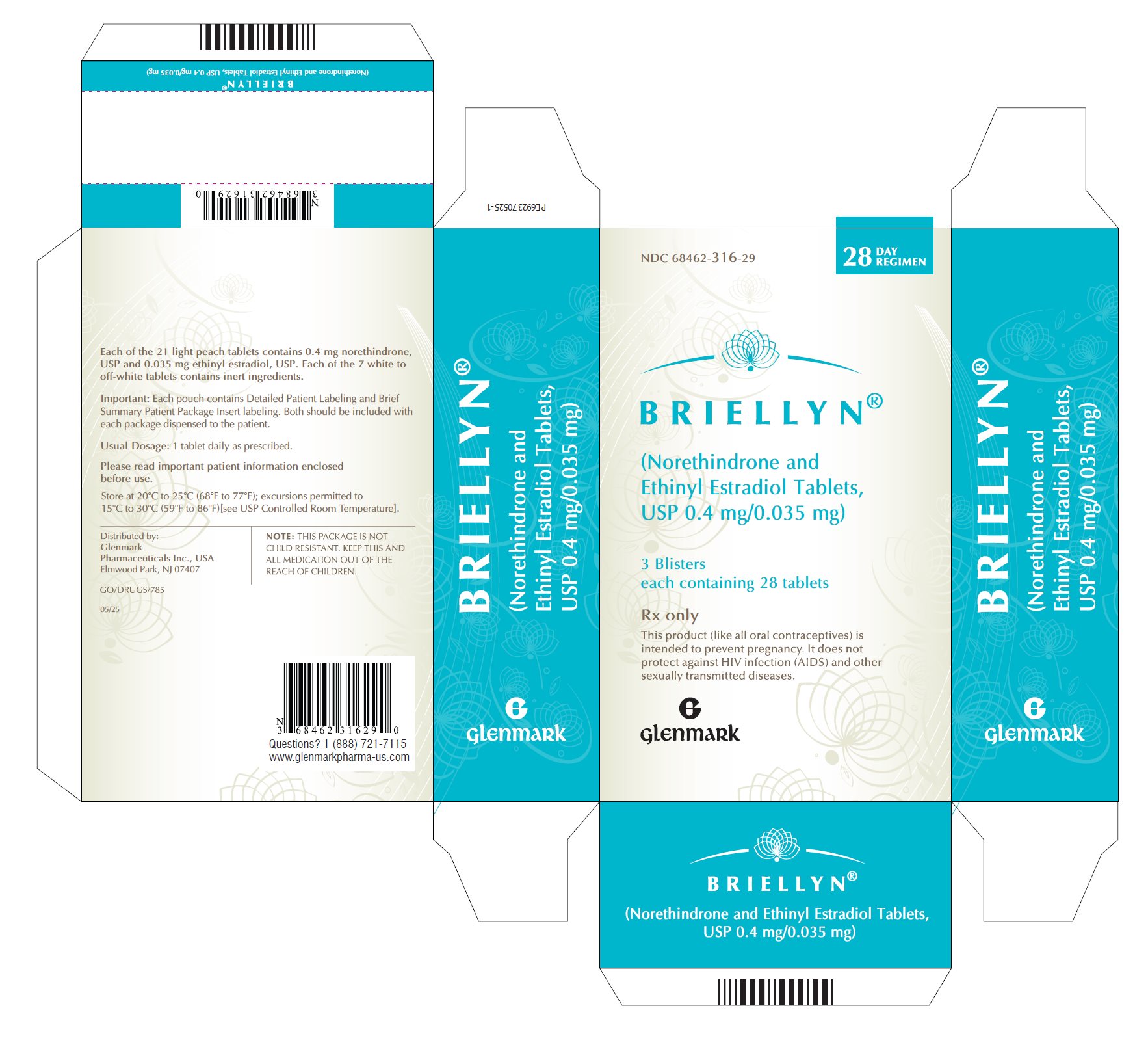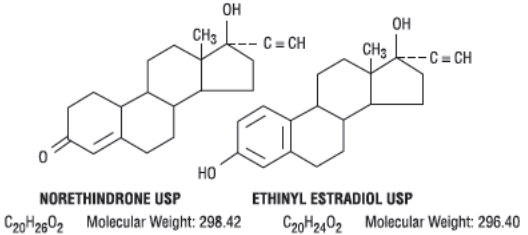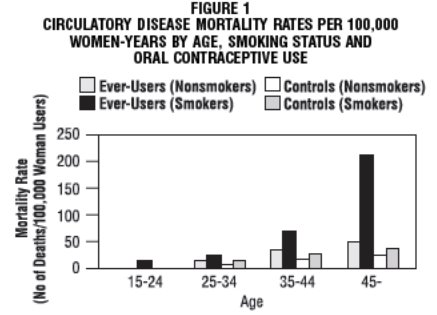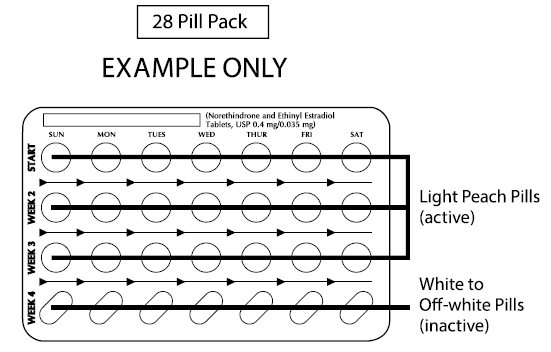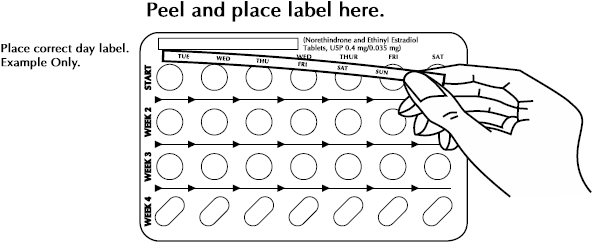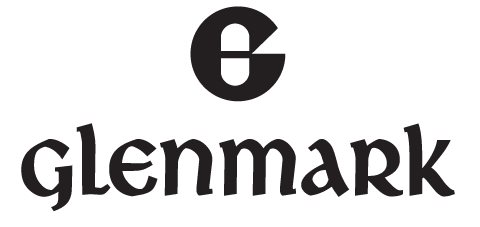 DRUG LABEL: BRIELLYN
NDC: 68462-316 | Form: KIT | Route: ORAL
Manufacturer: Glenmark Pharmaceuticals Inc., USA
Category: prescription | Type: HUMAN PRESCRIPTION DRUG LABEL
Date: 20260131

ACTIVE INGREDIENTS: NORETHINDRONE 0.4 mg/1 1; ETHINYL ESTRADIOL 0.035 mg/1 1
INACTIVE INGREDIENTS: ANHYDROUS LACTOSE; SILICON DIOXIDE; DIBASIC CALCIUM PHOSPHATE DIHYDRATE; FD&C YELLOW NO. 6; LACTOSE MONOHYDRATE; MAGNESIUM STEARATE; POVIDONE, UNSPECIFIED; SODIUM STARCH GLYCOLATE TYPE A POTATO; TALC; LACTOSE MONOHYDRATE; MAGNESIUM STEARATE; TALC

BRIELLYN® (Norethindrone and Ethinyl Estradiol Tablets, USP)

Rx only

Patients should be counseled that this product does not protect against HIV infection (AIDS) and other sexually transmitted diseases.

DESCRIPTION

BRIELLYN® 28-Day (norethindrone and ethinyl estradiol tablets, USP) provide a continuous regimen for oral contraception derived from 21 light peach tablets composed of norethindrone, USP and ethinyl estradiol, USP to be followed by 7 white to off-white tablets of inert ingredients. The structural formulas are:

The light peach active tablets each contain 0.4 mg norethindrone, USP and 0.035 mg ethinyl estradiol, USP and contain the following inactive ingredients: anhydrous lactose, colloidal silicon dioxide, dibasic calcium phosphate dihydrate, FD&C yellow no. 6 aluminum lake, lactose monohydrate, magnesium stearate, povidone, sodium starch glycolate and talc. The white to off-white tablets in the 28-Day regimen contain only inert ingredients as follows: lactose monohydrate, magnesium stearate, pregelatinized starch and talc.

CLINICAL PHARMACOLOGY

Combination oral contraceptives act by suppression of gonadotropins. Although the primary mechanism of this action is inhibition of ovulation, other alterations include changes in the cervical mucus (which increase the difficulty of sperm entry into the uterus) and the endometrium (which reduce the likelihood of implantation).

INDICATIONS AND USAGE

Oral contraceptives are indicated for the prevention of pregnancy in women who elect to use this product as a method of contraception.

Oral contraceptives are highly effective. Table 1 lists the typical accidental pregnancy rates for users of combination oral contraceptives and other methods of contraception. The efficacy of these contraceptive methods, except sterilization, depends upon the reliability with which they are used. Correct and consistent use of methods can result in lower failure rates.

TABLE 1: LOWEST EXPECTED AND TYPICAL FAILURE RATES DURING THE FIRST YEAR OF CONTINUOUS USE OF A METHOD
% of Women Experiencing an Accidental Pregnancy in the First Year of Continuous Use
Method | Lowest Expected* | Typical**
(No contraception) | (85) | (85)
Oral contraceptives
combined | 0.1 | 3***
progestin only | 0.5 | 3***
Diaphragm with spermicidal cream or jelly | 6 | 18
Spermicides alone (foam, creams, jellies and vaginal suppositories) | 3 | 21
Vaginal sponge
nulliparous | 6 | 18
multiparous | 9 | 28
IUD | 0.8-2.0 | 3#
Condom without spermicides | 2 | 12
Periodic abstinence (all methods) | 1-9 | 20
Injectable progestogen | 0.3-0.4 | 0.3-0.4
Implants
6 capsules | 0.04 | 0.04
2 rods | 0.03 | 0.03
Female sterilization | 0.2 | 0.4
Male sterilization | 0.1 | 0.15
Reproduced with permission of the Population Counsil from J. Trusell, et. al: Contraceptive failure in the United States: An update. Studies in Family Planning, 21(1), January-February 1990.
* The authors’ best guess of the percentage of women expected to experience an accidental pregnancy among couples who initiate a method (not necessarily for the first time) and who use it consistently and correctly during the first year if they do not stop for any reason other than pregnancy.
** This term represents “typical” couples who initiate use of a method (not necessarily for the first time), who experience an accidental pregnancy during the first year if they do not stop use for any reason other than pregnancy.
*** Combined typical rate for both combined and progestin only.
# Combined typical rate for both medicated and nonmedicated IUD.

CONTRAINDICATIONS

BRIELLYN is contraindicated in females who are known to have or develop the following conditions:

- Thrombophlebitis or thromboembolic disorders
- A past history of deep vein thrombophlebitis or thromboembolic disorders
- Cerebrovascular or coronary artery disease
- Current diagnosis of, or history of, breast cancer, which may be hormone-sensitive
- Carcinoma of the endometrium or other known or suspected estrogen-dependent neoplasia
- Undiagnosed abnormal genital bleeding
- Cholestatic jaundice of pregnancy or jaundice with prior pill use
- Hepatic adenomas or carcinomas
- Known or suspected pregnancy
- Are receiving Hepatitis C drug combinations containing ombitasvir/paritaprevir/ritonavir, with or without dasabuvir, due to the potential for ALT elevations (see WARNINGS, RISK OF LIVER ENZYME ELEVATIONS WITH CONCOMITANT HEPATITIS C TREATMENT).

WARNINGS

Cigarette smoking increases the risk of serious cardiovascular side effects from oral contraceptive use. This risk increases with age and with heavy smoking (15 or more cigarettes per day) and is quite marked in women over 35 years of age. Women who use oral contraceptives should be strongly advised not to smoke.

The use of oral contraceptives is associated with increased risk of several serious conditions including myocardial infarction, thromboembolism, stroke, hepatic neoplasia, and gallbladder disease, although the risk of serious morbidity or mortality is very small in healthy women without underlying risk factors. The risk of morbidity and mortality increases significantly in the presence of other underlying risk factors such as hypertension, hyperlipidemias, obesity and diabetes.

Practitioners prescribing oral contraceptives should be familiar with the following information relating to these risks.

The information contained in this package insert is principally based on studies carried out in patients who used oral contraceptives with higher formulations of estrogens and progestogens than those in common use today. The effect of long-term use of the oral contraceptives with lower formulations of both estrogens and progestogens remains to be determined.

Throughout this labeling, epidemiological studies reported are of two types: retrospective or case control studies and prospective or cohort studies. Case control studies provide a measure of the relative risk of a disease, namely, a ratio of the incidence of a disease among oral contraceptive users to that among nonusers. The relative risk does not provide information on the actual clinical occurrence of a disease. Cohort studies provide a measure of attributable risk, which is the difference in the incidence of disease between oral contraceptive users and nonusers. The attributable risk does provide information about the actual occurrence of a disease in the population*. For further information, the reader is referred to a text on epidemiological methods.

*Adapted from Stadel BB: Oral contraceptives and cardiovascular disease. N Engl J Med, 1981; 305: 612-618, 672-677; with author’s permission.

1. Thromboembolic Disorders and Other Vascular Problems:

The physician should be alert to the earliest manifestations of thromboembolic thrombotic disorders as discussed below. Should any of these occur or be suspected the drug should be discontinued immediately.

a. Myocardial Infarction:

An increased risk of myocardial infarction has been attributed to oral contraceptive use. This risk is primarily in smokers or women with other underlying risk factors for coronary artery disease such as hypertension, hypercholesterolemia, morbid obesity, and diabetes. The relative risk of heart attack for current oral contraceptive users has been estimated to be two to six. The risk is very low under the age of 30.

Smoking in combination with oral contraceptive use has been shown to contribute substantially to the incidence of myocardial infarctions in women in their mid-thirties or older, with smoking accounting for the majority of excess cases. Mortality rates associated with circulatory disease have been shown to increase substantially in smokers over the age of 35 and nonsmokers over the age of 40 (Figure 1) among women who use oral contraceptives.

Layde PM, Beral V: Further analyses of mortality in oral contraceptive users: Royal College of General Practitioners’ oral contraception study. (Table 5) Lancet 1981; 1:541-546.

Oral contraceptives may compound the effects of well-known risk factors, such as hypertension, diabetes, hyperlipidemias, age and obesity. In particular, some progestogens are known to decrease HDL cholesterol and cause glucose intolerance, while estrogens may create a state of hyperinsulinism. Oral contraceptives have been shown to increase blood pressure among users (see section 9 in WARNINGS). Such increases in risk factors have been associated with an increased risk of heart disease and the risk increases with the number of risk factors present. Oral contraceptives must be used with caution in women with cardiovascular disease risk factors.

b. Thromboembolism:

An increased risk of thromboembolic and thrombotic disease associated with the use of oral contraceptives is well established. Case control studies have found the relative risk of users compared to non-users to be 3 for the first episode of superficial venous thrombosis, 4 to 11 for deep vein thrombosis or pulmonary embolism, and 1.5 to 6 for women with predisposing conditions for venous thromboembolic disease. Cohort studies have shown the relative risk to be somewhat lower, about 3 for new cases and about 4.5 for new cases requiring hospitalization. The risk of thromboembolic disease due to oral contraceptives is not related to length of use and disappears after pill use is stopped.

A two- to four -fold increase in relative risk of postoperative thromboembolic complications has been reported with the use of oral contraceptives. The relative risk of venous thrombosis in women who have predisposing conditions is twice that of women without such medical conditions. If feasible, oral contraceptives should be discontinued at least four weeks prior to and for two weeks after elective surgery of a type associated with an increase in risk of thromboembolism and during and following prolonged immobilization. Since the immediate postpartum period is also associated with an increased risk of thromboembolism, oral contraceptives should be started no earlier than four to six weeks after delivery in women who elect not to breastfeed.

c. Cerebrovascular Diseases:

Oral contraceptives have been shown to increase both the relative and attributable risk of cerebrovascular events (thrombotic and hemorrhagic strokes); although, in general, the risk is greatest among older (>35 years), hypertensive women who also smoke. Hypertension was found to be a risk factor for both users and non-users, for both types of strokes, while smoking interacted to increase the risk for hemorrhagic strokes.

In a large study, the relative risk of thrombotic strokes has been shown to range from 3 for normotensive users to 14 for users with severe hypertension. The relative risk of hemorrhagic stroke is reported to be 1.2 for nonsmokers who used oral contraceptives, 2.6 for smokers who did not use oral contraceptives, 7.6 for smokers who used oral contraceptives, 1.8 for normotensive users and 25.7 for users with severe hypertension. The attributable risk is also greater in older women.

d. Dose-Related Risk of Vascular Disease from Oral Contraceptives:

A positive association has been observed between the amount of estrogen and progestogen in oral contraceptives and the risk of vascular disease. A decline in serum high density lipoproteins (HDL) has been reported with many progestational agents. A decline in serum high density lipoproteins has been associated with an increased incidence of ischemic heart disease. Because estrogens increase HDL cholesterol, the net effect of an oral contraceptive depends on a balance achieved between doses of estrogen and progestogen and the nature and absolute amount of progestogens used in the contraceptive. The amount of both hormones should be considered in the choice of an oral contraceptive.

Minimizing exposure to estrogen and progestogen is in keeping with good principles of therapeutics. For any particular estrogen/progestogen combination, the dosage regimen prescribed should be one which contains the least amount of estrogen and progestogen that is compatible with a low failure rate and the needs of the individual patient. New acceptors of oral contraceptive agents should be started on preparations containing 0.05 mg or less of estrogen.

e. Persistence of Risk:

There are two studies which have shown persistence of risk of vascular disease for ever-users of oral contraceptives. In a study in the United States, the risk of developing myocardial infarction after discontinuing oral contraceptives persists for at least 9 years for women 40-49 years old who had used oral contraceptives for five or more years, but this increased risk was not demonstrated in other age groups. In another study in Great Britain, the risk of developing cerebrovascular disease persisted for at least six years after discontinuation of oral contraceptives, although excess risk was very small. However, both studies were performed with oral contraceptive formulations containing 50 micrograms or higher of estrogens.

2. Estimates of Mortality from Contraceptive Use:

One study gathered data from a variety of sources which have estimated the mortality rate associated with different methods of contraception at different ages (Table 2).

TABLE 2: ANNUAL NUMBER OF BIRTH-RELATED OR METHOD-RELATED DEATHS ASSOCIATED WITH CONTROL OF FERTILITY PER 100,000 NONSTERILE WOMEN, BY FERTILITY CONTROL METHOD ACCORDING TO AGE
 | AGE
Method of control and outcome | 15-19 | 20-24 | 25-29 | 30-34 | 35-39 | 40-44
No fertility control methods* | 7.0 | 7.4 | 9.1 | 14.8 | 25.7 | 28.2
Oral contraceptives nonsmokers** | 0.3 | 0.5 | 0.9 | 1.9 | 13.8 | 31.6
Oral contraceptives smokers** | 2.2 | 3.4 | 6.6 | 13.5 | 51.1 | 117.2
IUD** | 0.8 | 0.8 | 1.0 | 1.0 | 1.4 | 1.4
Condom* | 1.1 | 1.6 | 0.7 | 0.2 | 0.3 | 0.4
Diaphragm/spermicides* | 1.9 | 1.2 | 1.2 | 1.3 | 2.2 | 2.8
Periodic abstinence* | 2.5 | 1.6 | 1.6 | 1.7 | 2.9 | 3.6
Ory HW: Mortality associated with fertility and fertility control: 1983. Fam Plann Perspect 1983; 15:50-56

*Deaths are birth related.

**Deaths are method related.

These estimates include the combined risk of death associated with contraceptive methods plus the risk attributable to pregnancy in the event of method failure. Each method of contraception has its specific benefits and risk. The study concluded that with the exception of oral contraceptive users 35 and older who smoke and 40 and older who do not smoke, mortality associated with all methods of birth control is low and below that associated with childbirth.

The observation of a possible increase in risk of mortality with age for oral contraceptive users is based on data gathered in the 1970’s - but not reported until 1983. However, current clinical practice involves the use of lower estrogen dose formulations combined with careful restriction of oral contraceptive use to women who do not have the various risk factors listed in this labeling.

Because of these changes in practice and, also, because of some limited new data which suggest that the risk of cardiovascular disease with the use of oral contraceptives may now be less than previously observed (Porter JB, Hunter J, Jick H, et al. Oral contraceptives and nonfatal vascular disease. Obstet Gynecol 1985; 66:1-4 and Porter JB, Jick H, Walker AM. Mortality among oral contraceptive users. Obstet Gynecol 1987; 70:29-32), the Fertility and Maternal Health Drugs Advisory Committee was asked to review the topic in 1989. The Committee concluded that although cardiovascular disease risk may be increased with oral contraceptive use after age 40 in healthy nonsmoking women (even with the newer low- dose formulations), there are greater potential health risks associated with pregnancy in older women and with the alternative surgical and medical procedures which may be necessary if such women do not have access to effective and acceptable means of contraception.

Therefore, the Committee recommended that the benefits of oral contraceptive use by healthy nonsmoking women over 40 may outweigh the possible risks. Of course, older women, as all women who take oral contraceptives, should take the lowest possible dose formulation that is effective.

3. Malignant Neoplasms:

Breast Cancer

BRIELLYN is contraindicated in females who currently have or have had breast cancer because breast cancer may be hormonally sensitive [see Contraindications]. Epidemiology studies have not found a consistent association between use of combined oral contraceptives (COCs) and breast cancer risk. Studies do not show an association between ever (current or past) use of COCs and risk of breast cancer. However, some studies report a small increase in the risk of breast cancer among current or recent users (<6 months since last use) and current users with longer duration of COC use [see Postmarketing Experience].

Cervical Cancer

Some studies suggest that oral contraceptive use has been associated with an increase in the risk of cervical intraepithelial neoplasia in some populations of women.

However, there continues to be controversy about the extent to which such findings may be due to differences in sexual behavior and other factors.

In spite of many studies of the relationship between oral contraceptive use and breast cancer and cervical cancers, a cause-and-effect relationship has not been established.

4. Hepatic Neoplasia:

Benign hepatic adenomas are associated with oral contraceptive use, although their occurrence is rare in the United States. Indirect calculations have estimated the attributable risk to be in the range of 3.3 cases/100,000 for users, a risk that increases after four or more years of use. Rupture of hepatic adenomas may cause death through intra-abdominal hemorrhage.

Studies from Britain have shown an increased risk of developing hepatocellular carcinoma in long-term (>8 years) oral contraceptive users. However, these cancers are extremely rare in the U.S. and the attributable risk (the excess incidence) of liver cancers in oral contraceptive users approaches less than one per million users.

RISK OF LIVER ENZYME ELEVATIONS WITH CONCOMITANT HEPATITIS C TREATMENT

During clinical trials with the Hepatitis C combination drug regimen that contains ombitasvir/paritaprevir/ritonavir, with or without dasabuvir, ALT elevations greater than 5 times the upper limit of normal (ULN), including some cases greater than 20 times the ULN, were significantly more frequent in women using ethinyl estradiol-containing medications such as COCs. Discontinue BRIELLYN prior to starting therapy with the combination drug regimen ombitasvir/paritaprevir/ritonavir, with or without dasabuvir [see CONTRAINDICATIONS (4)]. BRIELLYN can be restarted approximately 2 weeks following completion of treatment with the combination drug regimen.

5. Ocular Lesions:

There have been clinical case reports of retinal thrombosis associated with the use of oral contraceptives. Oral contraceptives should be discontinued if there is unexplained partial or complete loss of vision; onset of proptosis or diplopia; papilledema; or retinal vascular lesions. Appropriate diagnostic and therapeutic measures should be undertaken immediately.

6. Oral Contraceptive Use Before or During Early Pregnancy:

Extensive epidemiological studies have revealed no increased risk of birth defects in women who have used oral contraceptives prior to pregnancy. Studies also do not suggest a teratogenic effect, particularly in so far as cardiac anomalies and limb reduction defects are concerned, when taken inadvertently during early pregnancy.

The administration of oral contraceptives to induce withdrawal bleeding should not be used as a test for pregnancy. Oral contraceptives should not be used during pregnancy to treat threatened or habitual abortion.

It is recommended that for any patient who has missed two consecutive periods, pregnancy should be ruled out before continuing oral contraceptive use. If the patient has not adhered to the prescribed schedule, the possibility of pregnancy should be considered at the time of the first missed period. Oral contraceptive use should be discontinued if pregnancy is confirmed.

7. Gallbladder Disease:

Earlier studies have reported an increased lifetime relative risk of gallbladder surgery in users of oral contraceptives and estrogens. More recent studies, however, have shown that the relative risk of developing gallbladder disease among oral contraceptive users may be minimal.

The recent findings of minimal risk may be related to the use of oral contraceptive formulations containing lower hormonal doses of estrogens and progestogens.

8. Carbohydrate and Lipid Metabolic Effects:

Oral contraceptives have been shown to cause glucose intolerance in a significant percentage of users. Oral contraceptives containing greater than 75 micrograms of estrogens cause hyperinsulinism, while lower doses of estrogen cause less glucose intolerance. Progestogens increase insulin secretion and create insulin resistance, this effect varying with different progestational agents.

However, in the nondiabetic woman, oral contraceptives appear to have no effect on fasting blood glucose. Because of these demonstrated effects, prediabetic and diabetic women should be carefully observed while taking oral contraceptives.

A small proportion of women will have persistent hypertriglyceridemia while on the pill. As discussed earlier (see WARNINGS, 1a and 1d), changes in serum triglycerides and lipoprotein levels have been reported in oral contraceptive users.

9. Elevated Blood Pressure:

An increase in blood pressure has been reported in women taking oral contraceptives and this increase is more likely in older oral contraceptive users and with continued use. Data from the Royal College of General Practitioners and subsequent randomized trials have shown that the incidence of hypertension increases with increasing concentrations of progestogens.

Women with a history of hypertension or hypertension-related diseases, or renal disease should be encouraged to use another method of contraception. If women elect to use oral contraceptives, they should be monitored closely and if significant elevation of blood pressure occurs, oral contraceptives should be discontinued. For most women, elevated blood pressure will return to normal after stopping oral contraceptives, and there is no difference in the occurrence of hypertension among ever- and never-users.

10. Headache:

The onset or exacerbation of migraine or development of headache with a new pattern which is recurrent, persistent or severe requires discontinuation of oral contraceptives and evaluation of the cause.

11. Bleeding Irregularities:

Breakthrough bleeding and spotting are sometimes encountered in patients on oral contraceptives, especially during the first three months of use. Nonhormonal causes should be considered and adequate diagnostic measures taken to rule out malignancy or pregnancy in the event of breakthrough bleeding, as in the case of any abnormal vaginal bleeding. If pathology has been excluded, time or a change to another formulation may solve the problem. In the event of amenorrhea, pregnancy should be ruled out.

Women with a history of oligomenorrhea or secondary amenorrhea or young women without regular cycles prior to taking oral contraceptives may again have irregular bleeding or amenorrhea after discontinuation of oral contraceptives.

PRECAUTIONS

1. Sexually -Transmitted Diseases:

Patients should be counseled that this product does not protect against HIV infection (AIDS) and other sexually transmitted diseases.

2. Physical Examination and Follow-Up:

It is good medical practice for all women to have annual history and physical examinations, including women using oral contraceptives. The physical examination, however, may be deferred until after initiation of oral contraceptives if requested by the woman and judged appropriate by the clinician. The physical examination should include special reference to blood pressure, breasts, abdomen and pelvic organs, including cervical cytology, and relevant laboratory tests. In case of undiagnosed, persistent or recurrent abnormal vaginal bleeding, appropriate measures should be conducted to rule out malignancy. Women with a strong family history of breast cancer or who have breast nodules should be monitored with particular care.

3. Lipid Disorders:

Women who are being treated for hyperlipidemias should be followed closely if they elect to use oral contraceptives. Some progestogens may elevate LDL levels and may render the control of hyperlipidemias more difficult.

4. Liver Function:

If jaundice develops in any woman receiving such drugs, the medication should be discontinued. Steroid hormones may be poorly metabolized in patients with impaired liver function.

5. Fluid Retention:

Oral contraceptives may cause some degree of fluid retention. They should be prescribed with caution, and only with careful monitoring, in patients with conditions which might be aggravated by fluid retention.

6. Emotional Disorders:

Women with a history of depression should be carefully observed and the drug discontinued if depression recurs to a serious degree.

Patients becoming significantly depressed while taking oral contraceptives should stop the medication and use an alternate method of contraception in an attempt to determine whether the symptom is drug related.

7. Contact Lenses:

Contact lens wearers who develop visual changes or changes in lens tolerance should be assessed by an ophthalmologist.

8. Drug Interactions:

Reduced efficacy and increased incidence of breakthrough bleeding and menstrual irregularities have been associated with concomitant use of rifampin. A similar association, though less marked, has been suggested with barbiturates, phenylbutazone, phenytoin sodium, and possibly with griseofulvin, ampicillin, and tetracyclines.

Concomitant Use with HCV Combination Therapy - Liver Enzyme Elevation

Do not co-administer BRIELLYN with HCV drug combinations containing ombitasvir/paritaprevir/ritonavir, with or without dasabuvir, due to potential for ALT elevations (see WARNINGS, RISK OF LIVER ENZYME ELEVATIONS WITH CONCOMITANT HEPATITIS C TREATMENT).

9. Interactions with Laboratory Tests:

Certain endocrine and liver function tests and blood components may be affected by oral contraceptives:

a. Increased prothrombin and factors VII, VIII, IX, and X; decreased antithrombin 3; increased norepinephrine-induced platelet aggregability.

b. Increased thyroid-binding globulin (TBG) leading to increased circulating total thyroid hormone, as measured by protein-bound iodine (PBI), T4 by column or by radioimmunoassay. Free T3 resin uptake is decreased, reflecting the elevated TBG; free T4 concentration is unaltered.

c. Other binding proteins may be elevated in serum.

d. Sex-binding globulins are increased and result in elevated levels of total circulating sex steroids and corticoids; however, free or biologically active levels remain unchanged.

e. Triglycerides may be increased.

f. Glucose tolerance may be decreased.

g. Serum folate levels may be depressed by oral contraceptive therapy. This may be of clinical significance if a woman becomes pregnant shortly after discontinuing oral contraceptives.

10. Carcinogenesis:

See WARNINGS section.

11. Pregnancy:

See CONTRAINDICATIONS and WARNINGS sections.

12. Nursing Mothers:

Small amounts of oral contraceptive steroids have been identified in the milk of nursing mothers and a few adverse effects on the child have been reported, including jaundice and breast enlargement. In addition, oral contraceptives given in the postpartum period may interfere with lactation by decreasing the quantity and quality of breast milk. If possible, the nursing mother should be advised not to use oral contraceptives but to use other forms of contraception until she has completely weaned her child.

13. Vomiting and/or Diarrhea:

Although a cause-and-effect relationship has not been clearly established, several cases of oral contraceptive failure have been reported in association with vomiting and/or diarrhea. If significant gastrointestinal disturbance occurs in any woman receiving contraceptive steroids, the use of a back-up method of contraception for the remainder of that cycle is recommended.

14. Pediatric Use:

Safety and efficacy of BRIELLYN (norethindrone and ethinyl estradiol tablets, USP) have been established in women of reproductive age. Safety and efficacy are expected to be the same in post-pubertal adolescents under the age of 16 years and in users ages 16 years and older. Use of this product before menarche is not indicated.

Information for Patients

See patient labeling printed below.

ADVERSE REACTIONS

An increased risk of the following serious adverse reactions has been associated with the use of oral contraceptives (see WARNINGS section):

- Thrombophlebitis
- Arterial thromboembolism
- Pulmonary embolism
- Myocardial infarction
- Cerebral hemorrhage
- Cerebral thrombosis
- Hypertension
- Gallbladder disease
- Hepatic adenomas or benign liver tumors

There is evidence of an association between the following conditions and the use of oral contraceptives, although additional confirmatory studies are needed:

- Mesenteric thrombosis
- Retinal thrombosis

The following adverse reactions have been reported in patients receiving oral contraceptives and are believed to be drug-related:

- Nausea
- Vomiting
- Gastrointestinal symptoms (such as abdominal cramps and bloating)
- Breakthrough bleeding
- Spotting
- Change in menstrual flow
- Amenorrhea
- Temporary infertility after discontinuation of treatment
- Edema
- Melasma which may persist
- Breast changes: tenderness, enlargement, and secretion
- Change in weight (increase or decrease)
- Change in cervical ectropion and secretion
- Possible diminution in lactation when given immediately postpartum
- Cholestatic jaundice
- Migraine
- Rash (allergic)
- Mental depression
- Reduced tolerance to carbohydrates
- Vaginal candidiasis
- Change in corneal curvature (steepening)
- Intolerance to contact lenses

The following adverse reactions have been reported in users of oral contraceptives, and the association has been neither confirmed nor refuted:

- Premenstrual syndrome
- Cataracts
- Changes in appetite
- Cystitis-like syndrome
- Headache
- Nervousness
- Dizziness
- Hirsutism
- Loss of scalp hair
- Erythema multiforme
- Erythema nodosum
- Hemorrhagic eruption
- Vaginitis
- Porphyria
- Impaired renal function
- Hemolytic uremic syndrome
- Budd-Chiari syndrome
- Acne
- Changes in libido
- Colitis

Post Marketing Experience:

Five studies that compared breast cancer risk between ever-users (current or past use) of COCs and never-users of COCs reported no association between ever use of COCs and breast cancer risk, with effect estimates ranging from 0.90 to 1.12 (Figure 2).

Three studies compared breast cancer risk between current or recent COC users (<6 months since last use) and never users of COCs (Figure 2). One of these studies reported no association between breast cancer risk and COC use. The other two studies found an increased relative risk of 1.19 to 1.33 with current or recent use. Both of these studies found an increased risk of breast cancer with current use of longer duration, with relative risks ranging from 1.03 with less than one year of COC use to approximately 1.4 with more than 8 to 10 years of COC use.

Figure 2

RR = relative risk; OR = odds ratio; HR = hazard ratio. “ever COC” are females with current or past COC use; “never COC use” are females that never used COCs.

OVERDOSAGE

Serious ill effects have not been reported following acute ingestion of large doses of oral contraceptives by young children. Overdosage may cause nausea, and withdrawal bleeding may occur in females.

NONCONTRACEPTIVE HEALTH BENEFITS:

The following noncontraceptive health benefits related to the use of oral contraceptives are supported by epidemiological studies which largely utilized oral contraceptive formulations containing estrogen doses exceeding 0.035 mg of ethinyl estradiol or 0.05 mg of mestranol.

Effects on menses:

- Increased menstrual cycle regularity
- Decreased blood loss and decreased incidence of iron deficiency anemia
- Decreased incidence of dysmenorrhea

Effects related to inhibition of ovulation:

- Decreased incidence of functional ovarian cysts
- Decreased incidence of ectopic pregnancies

Effects from long-term use:

- Decreased incidence of fibroadenomas and fibrocystic disease of the breast
- Decreased incidence of acute pelvic inflammatory disease
- Decreased incidence of endometrial cancer
- Decreased incidence of ovarian cancer

DOSAGE AND ADMINISTRATION

The following is a summary of the instructions given to the patient in the “HOW TO TAKE THE PILL” section of the DETAILED PATIENT LABELING.

The patient is given instructions in five (5) categories:

1. IMPORTANT POINTS TO REMEMBER: The patient is told (a) that she should take one pill every day at the same time, (b) many women have spotting or light bleeding or gastric distress during the first one to three cycles, (c) missing pills can also cause spotting or light bleeding, (d) she should use a back-up method for contraception if she has vomiting or diarrhea or takes some concomitant medications, and/or if she has trouble remembering the pill, (e) if she has any other questions, she should consult her physician.

2. BEFORE SHE STARTS TAKING HER PILLS: She should decide what time of day she wishes to take the pill, check whether her pill pack has 28 pills, and note the order in which she should take the pills (diagrammatic drawings of the pill pack are included in the patient insert).

3. WHEN SHE SHOULD START THE FIRST PACK: The Day-One start is listed as the first choice and the Sunday start (the Sunday after her period starts) is given as the second choice. If she uses the Sunday start she should use a back-up method in the first cycle if she has intercourse before she has taken seven pills.

4. WHAT TO DO DURING THE CYCLE: The patient is advised to take one pill at the same time every day until the pack is empty. If she is on the 28 day regimen, she should start the next pack the day after the last inactive tablet and not wait any days between packs.

5. WHAT TO DO IF SHE MISSES A PILL OR PILLS: The patient is given instructions about what she should do if she misses one, two or more than two pills at varying times in her cycle for both the Day-One and the Sunday start. The patient is warned that she may become pregnant if she has unprotected intercourse in the seven days after missing pills. To avoid this, she must use another birth control method such as condom, foam, or sponge in these seven days.

HOW SUPPLIED

BRIELLYN 28-Day (Norethindrone and Ethinyl Estradiol Tablets, USP 0.4 mg/0.035 mg) are available in cartons (NDC 68462-316-29) of 3 blisters (NDC 68462-316-84) each containing 28 tablets.

Each blister contains:

21 active tablets: Light peach, round, flat faced, beveled-edged, uncoated tablets with ‘316’ debossed on one side and ‘G’ on the other side.

7 Inert tablets: White to off-white, capsule-shaped, biconvex, uncoated tablet with ‘317’ debossed on one side and ‘G’ on the other side.

Store at 20°C to 25°C (68°F to 77°F) [see USP Controlled Room Temperature].

References are available upon request.

Distributed by:

Glenmark Pharmaceuticals Inc., USA

Elmwood Park, NJ 07407

Questions? 1 (888) 721-7115

www.glenmarkpharma-us.com

May 2025

BRIEF SUMMARY PATIENT PACKAGE INSERT

This product (like all oral contraceptives) is intended to prevent pregnancy. It does not protect against HIV infection (AIDS) and other sexually transmitted diseases.

Oral contraceptives, also known as “birth control pills” or “the pill,” are taken to prevent pregnancy and when taken correctly, have a failure rate of about 1% per year when used without missing any pills. The typical failure rate of large numbers of pill users is less than 3% per year when women who miss pills are included.

Oral contraceptive use is associated with certain serious diseases that can be life-threatening or may cause temporary or permanent disability. The risks associated with taking oral contraceptives increase significantly if you:

- Smoke
- Have high blood pressure, diabetes, high cholesterol
- Have or have had clotting disorders, heart attack, stroke, angina pectoris, cancer of the breast or sex organs, jaundice or malignant or benign liver tumors.

You should not take the pill if you suspect you are pregnant or have unexplained vaginal bleeding.

Cigarette smoking increases the risk of serious cardiovascular side effects from oral contraceptive use. This risk increases with age and with heavy smoking (15 or more cigarettes per day) and is quite marked in women over 35 years of age. Women who use oral contraceptives should be strongly advised not to smoke.

Most side effects of the pill are not serious. The most common side effects are nausea, vomiting, bleeding between menstrual periods, weight gain, breast tenderness, and difficulty wearing contact lenses. These side effects, especially nausea and vomiting, may subside within the first three months of use.

The serious side effects of the pill occur very infrequently, especially if you are in good health and are young. However, you should know that the following medical conditions have been associated with or made worse by the pill:

1. Blood clots in the legs (thrombophlebitis), lungs (pulmonary embolism), stoppage or rupture of a blood vessel in the brain (stroke), blockage of blood vessels in the heart (heart attack or angina pectoris), or other organs of the body. As mentioned above, smoking increases the risk of heart attacks and strokes and subsequent serious medical consequences.

2. Liver tumors, which may rupture and cause severe bleeding. A possible but not definite association has been found with the pill and liver cancer. However, liver cancers are extremely rare. The chance of developing liver cancer from using the pill is thus even rarer.

3. High blood pressure, although blood pressure usually returns to normal when the pill is stopped.

The symptoms associated with these serious side effects are discussed in the detailed leaflet given to you with your supply of pills. Notify your doctor or health care provider if you notice any unusual physical disturbances while taking the pill. In addition, drugs such as rifampin, as well as some anticonvulsants and some antibiotics may decrease oral contraceptive effectiveness.

There may be slight increases in the risk of breast cancer among current users of hormonal birth control pills with longer duration of use of 8 years or more.

Taking the pill provides some important noncontraceptive effects. These include less painful menstruation, less menstrual blood loss and anemia, fewer pelvic infections, and fewer cancers of the ovary and the lining of the uterus.

Be sure to discuss any medical condition you may have with your health care provider. Your health care provider will take a medical and family history before prescribing oral contraceptives and will examine you. The physical examination may be delayed to another time if you request it and the health care provider believes that it is a good medical practice to postpone it. You should be reexamined at least once a year while taking oral contraceptives. The detailed patient labeling gives you further information which you should read and discuss with your Heath care professional.

DOSAGE AND ADMINISTRATION:

HOW TO TAKE THE PILL:

The instructions given in the DETAILED PATIENT LABELING and BRIEF SUMMARY PATIENT PACKAGE INSERTare included inside the foil pouch. The instructions include the directions on starting the first pack on Day-One (first choice) of her period and the Sunday start (Sunday after period starts). The patient is advised that, if she used the Sunday start, she should use a back-up method in the first cycle if she has intercourse before she has taken seven pills. The patient is also instructed as to what she should do if she misses a pill or pills. The patient is warned that she may become pregnant if she misses a pill or pills and that she should use a back-up method of birth control in the event she has intercourse any time during the seven day period following the missed pill or pills.

Instructions on how to use the blister for the (28 Tablets) are included in the BRIEF SUMMARY PATIENT PACKAGE INSERT.

DETAILED PATIENT LABELING

This product (like all oral contraceptives) is intended to prevent pregnancy. It does not protect against HIV infection (AIDS) and other sexually transmitted diseases.

INTRODUCTION:

Any woman who considers using oral contraceptives (the “birth control pill” or the “pill”) should understand the benefits and risks of using this form of birth control.

Although the oral contraceptives have important advantages over other methods of contraception, they have certain risks that no other method has and some of these risks may continue after you have stopped using the oral contraceptive. This brochure will give you much of the information you will need to make this decision and will also help you determine if you are at risk of developing any of the serious side effects of the pill. It will tell you how to use the pill properly so that it will be as effective as possible. However, this brochure is not a replacement for a careful discussion between you and your health care professional.

You should discuss the information provided in this brochure with him or her, both when you first start taking the pill and during your revisits. You should also follow your health care professional’s advice with regard to regular check-ups while you are on the pill.

EFFECTIVENESS OF ORAL CONTRACEPTIVES:

Oral contraceptives or “birth control pills” or “the pill” are used to prevent pregnancy and are more effective than other nonsurgical methods of birth control. The chance of becoming pregnant is less than 1% (1 pregnancy per 100 women per year of use) when the pills are used correctly and no pills are missed. Typical failure rates are actually 3% per year. The chance of becoming pregnant increases with each missed pill during a menstrual cycle.

In comparison, typical accidental pregnancy rates for other nonsurgical methods of birth control during the first year of use are as follows:

IUD: 3%

Diaphragm with spermicides: 18%

Spermicides alone: 21%

Vaginal Sponge: 18% to 28%

Condom alone: 12%

Periodic abstinence: 20%

Injectable progestogen: 0.3% to 0.4%

Implants: 0.03% to 0.04%

No methods: 85%

WHO SHOULD NOT TAKE ORAL CONTRACEPTIVES:

Cigarette smoking increases the risk of serious cardiovascular side effects from oral contraceptive use. This risk increases with age and with heavy smoking (15 or more cigarettes per day) and is quite marked in women over 35 years of age. Women who use oral contraceptives should not smoke.

Some women should not use the pill. For example, you should not take the pill if you are pregnant or think you may be pregnant. You should also not use the pill if you have or have ever had any of the following conditions:

- A history of heart attack or stroke
- Blood clots in the legs (thrombophlebitis), lungs (pulmonary embolism), or eyes
- A history of blood clots in the deep veins of your legs
- Chest pain (angina pectoris)
- Known or suspected breast cancer or cancer of the lining of the uterus
- Unexplained vaginal bleeding (until a diagnosis is reached by your doctor)
- Yellowing of the whites of the eyes or of the skin (jaundice) during pregnancy or during previous use of the pill
- Liver tumor (benign or cancerous)
- Take any Hepatitis C drug combination containing ombitasvir/paritaprevir/ritonavir, with or without dasabuvir. This may increase levels of the liver enzyme "alanine aminotransferase" (ALT) in the blood.

Tell your health care professional if you have ever had any of these conditions. Your health care professional can recommend a safer method of birth control.

OTHER CONSIDERATIONS BEFORE TAKING ORAL CONTRACEPTIVES:

Tell your health care professional if you have:

- Breast nodules, fibrocystic disease of the breast or an abnormal breast x-ray or mammogram
- Diabetes
- Elevated cholesterol or triglycerides
- High blood pressure
- Migraine or other headaches or epilepsy
- Mental depression
- Gallbladder, heart or kidney disease
- History of scanty or irregular menstrual periods

Women with any of these conditions should be checked often by their health care professional if they choose to use oral contraceptives.

Also, be sure to inform your doctor or health care professional if you smoke or are on any medications.

RISKS OF TAKING ORAL CONTRACEPTIVES:

1. Risk of Developing Blood Clots:

Blood clots and blockage of blood vessels are the most serious side effects of taking oral contraceptives. In particular, a clot in the legs can cause thrombophlebitis and a clot that travels to the lungs can cause a sudden blocking of the vessel carrying blood to the lungs. Either of these can cause death or disability. Rarely, clots occur in the blood vessels of the eye and may cause blindness, double vision, or impaired vision.

If you take oral contraceptives and need elective surgery, need to stay in bed for a prolonged illness, or have recently delivered a baby, you may be at risk of developing blood clots. You should consult your doctor about stopping oral contraceptives three to four weeks before surgery and not taking oral contraceptives for two weeks after surgery or during bed rest. You should also not take oral contraceptives soon after delivery of a baby. It is advisable to wait for at least four weeks after delivery if you are not breastfeeding. If you are breastfeeding, see the section on Breastfeeding in GENERAL PRECAUTIONS.

2. Heart Attacks and Strokes:

Oral contraceptives may increase the tendency to develop strokes (stoppage or rupture of blood vessels in the brain) and angina pectoris and heart attacks (blockage of blood vessels in the heart). Any of these conditions can cause death or disability.

Smoking greatly increases the possibility of suffering heart attacks and strokes. Furthermore, smoking and the use of oral contraceptives greatly increase the chances of developing and dying of heart disease.

3. Gallbladder Disease:

Oral contraceptive users probably have a greater risk than nonusers of having gallbladder disease, although this risk may be related to pills containing high doses of estrogens.

4. Liver Tumors:

In rare cases, oral contraceptives can cause benign but dangerous liver tumors. These benign liver tumors can rupture and cause fatal internal bleeding. In addition, a possible, but not definite, association has been found with the pill and liver cancers in two studies, in which a few women who developed these very rare cancers were found to have used oral contraceptives for long periods. However, liver cancers in general are extremely rare and the chance of developing liver cancer from using the pill is thus even rarer.

5. Risk of Cancer:

It is not known if hormonal birth control pills cause breast cancer. Some studies, but not all, suggest that there could be a slight increase in the risk of breast cancer among current users with longer duration of use.

If you have breast cancer now, or have had it in the past, do not use hormonal birth control because some breast cancers are sensitive to hormones.

Some studies have found an increase in the incidence of cancer of the cervix in women who use oral contraceptives. However, this finding may be related to factors other than the use of oral contraceptives.

ESTIMATED RISK OF DEATH FROM A BIRTH CONTROL METHOD OR PREGNANCY:

All methods of birth control and pregnancy are associated with a risk of developing certain diseases which may lead to disability or death. An estimate of the number of deaths associated with different methods of birth control and pregnancy has been calculated and is shown in the following table.

ANNUAL NUMBER OF BIRTH-RELATED OR METHOD-RELATED DEATHSASSOCIATED WITH CONTROL OF FERTILITY PER 100,000 NONSTERILE WOMEN, BY FERTILITY CONTROL METHOD ACCORDING TO AGE
 | AGE
Method of control and outcome | 15-19 | 20-24 | 25-29 | 30-34 | 35-39 | 40-44
No fertility control methods* | 7.0 | 7.4 | 9.1 | 14.8 | 25.7 | 28.2
Oral contraceptives nonsmoker** | 0.3 | 0.5 | 0.9 | 1.9 | 13.8 | 31.6
Oral contraceptives smoker** | 2.2 | 3.4 | 6.6 | 13.5 | 51.1 | 117.2
IUD** | 0.8 | 0.8 | 1.0 | 1.0 | 1.4 | 1.4
Condom* | 1.1 | 1.6 | 0.7 | 0.2 | 0.3 | 0.4
Diaphragm/spermicide* | 1.9 | 1.2 | 1.2 | 1.3 | 2.2 | 2.8
Periodic abstinence* | 2.5 | 1.6 | 1.6 | 1.7 | 2.9 | 3.6
*Deaths are birth related
**Deaths are method related

It can be seen in the table that for women aged 15 to 39, the risk of death was highest with pregnancy (7-26 deaths per 100,000 women, depending on age). Among pill users who do not smoke, the risk of death was always lower than that associated with pregnancy for any age group, although over the age of 40, the risk increases to 32 deaths per 100,000 women, compared to 28 associated with pregnancy at that age. However, for pill users who smoke and are over the age of 35, the estimated number of deaths exceeds those for other methods of birth control. If a woman is over the age of 40 and smokes, her estimated risk of death is four times higher (117/100,000 women) than the estimated risk associated with pregnancy (28/100,000 women) in that age group.

The suggestion that women over 40 who don’t smoke should not take oral contraceptives is based on information from older high-dose pills and on less selective use of pills than is practiced today.

An Advisory Committee of the FDA discussed this issue in 1989 and recommended that the benefits of oral contraceptive use by healthy, nonsmoking women over 40 years of age may outweigh the possible risks. However, all women, especially older women, are cautioned to use the lowest dose pill that is effective.

In the above table, the risk of death from any birth control method is less than the risk of childbirth, except for oral contraceptive users over the age of 35 who smoke and pill users over the age of 40 even if they do not smoke.

You should discuss this information with your health care professional.

WARNING SIGNALS:

If any of these adverse conditions occur while you are taking oral contraceptives, call your doctor immediately:

- Sharp chest pain, coughing of blood, or sudden shortness of breath (indicating a possible clot in the lung)
- Pain in the calf (indicating a possible clot in the leg)
- Crushing chest pain or heaviness in the chest (indicating a possible heart attack)
- Sudden severe headache or vomiting, dizziness or fainting, disturbances of vision or speech, weakness, or numbness in an arm or leg (indicating a possible stroke)
- Sudden partial or complete loss of vision (indicating a possible clot in the eye)
- Breast lumps (indicating possible breast cancer or fibrocystic disease of the breast; ask your doctor or health care provider to show you how to examine your breasts)
- Severe pain or tenderness in the stomach area (indicating a possibly ruptured liver tumor)
- Difficulty in sleeping, weakness, lack of energy, fatigue, or change in mood (possibly indicating severe depression)
- Jaundice or a yellowing of the skin or eyeballs, accompanied frequently by fever, fatigue, loss of appetite, dark-colored urine, or light-colored bowel movements (indicating possible liver problems)
- Abnormal vaginal bleeding (see SIDE EFFECTS OF ORAL CONTRACEPTIVES, 1. Vaginal Bleeding below).

SIDE EFFECTS OF ORAL CONTRACEPTIVES:

In addition to the risks and more serious side effects discussed above (see RISKS OF TAKING ORAL CONTRACEPTIVES, ESTIMATED RISK OF DEATH FROM A BIRTH CONTROL METHOD OR PREGNANCY and WARNING SIGNALS sections above), the following may also occur:

1. Vaginal Bleeding:

Irregular vaginal bleeding or spotting may occur while you are taking the pills. Irregular bleeding may vary from slight staining between menstrual periods to breakthrough bleeding which is a flow much like a regular period. Irregular bleeding occurs most often during the first few months of oral contraceptive use, but may also occur after you have been taking the pill for some time. Such bleeding may be temporary and usually does not indicate any serious problems. It is important to continue taking your pills on schedule. If the bleeding occurs in more than one cycle or lasts for more than a few days, talk to your doctor or health care provider.

2. Gastrointestinal Effects:

The most frequent, unpleasant side effects are nausea and vomiting, stomach cramps, bloating, and a change in appetite.

3. Contact Lenses:

If you wear contact lenses and notice a change in vision or an inability to wear your lenses, contact your doctor or health care provider.

4. Fluid Retention:

Oral contraceptives may cause edema (fluid retention) with swelling of the fingers or ankles and may raise your blood pressure. If you experience fluid retention, contact your doctor or health care professional.

5. Melasma:

A spotty darkening of the skin is possible, particularly of the face.

6. Other Side Effects:

Other side effects may include change in appetite, headache, nervousness, depression, dizziness, loss of scalp hair, rash, and vaginal infections.

If any of these side effects bother you, call your doctor or health care professional.

GENERAL PRECAUTIONS:

1. Missed Periods and Use of Oral Contraceptives Before or During Early Pregnancy:

There may be times when you may not menstruate regularly after you have completed taking a cycle of pills. If you have taken your pills regularly and miss one menstrual period, continue taking your pills for the next cycle but be sure to inform your health care professional before doing so. If you have not taken the pills daily as instructed and missed a menstrual period, or if you missed two consecutive menstrual periods, you may be pregnant. Check with your health care professional immediately to determine whether you are pregnant. Do not continue to take oral contraceptives until you are sure you are not pregnant, but continue to use another method of contraception.

There is no conclusive evidence that oral contraceptive use is associated with an increase in birth defects, when taken inadvertently during early pregnancy. Previously, a few studies had reported that oral contraceptives might be associated with birth defects, but these studies have not been confirmed. Nevertheless, oral contraceptives or any other drugs should not be used during pregnancy unless clearly necessary and prescribed by your doctor. You should check with your doctor about risks to your unborn child of any medication taken during pregnancy.

2. While Breastfeeding:

If you are breastfeeding, consult your doctor before starting oral contraceptives. Some of the drug will be passed on to the child in the milk. A few adverse effects on the child have been reported, including yellowing of the skin (jaundice) and breast enlargement. In addition, oral contraceptives may decrease the amount and quality of your milk. If possible, do not use oral contraceptives while breast feeding. You should use another method of contraception since breastfeeding provides only partial protection from becoming pregnant and this partial protection decreases significantly as you breastfeed for longer periods of time. You should consider starting oral contraceptives only after you have weaned your child completely.

3. Laboratory Tests:

If you are scheduled for any laboratory tests, tell your doctor you are taking birth control pills. Certain blood tests may be affected by birth control pills.

4. Drug Interactions:

Certain drugs may interact with birth control pills to make them less effective in preventing pregnancy or cause an increase in breakthrough bleeding. Such drugs include rifampin, drugs used for epilepsy such as barbiturates (for example, phenobarbital) and phenytoin (Dilantin is one brand of this drug), phenylbutazone (Butazolidin is one brand) and possibly ampicillin and tetracyclines (several brand names). You may need to use an additional method of contraception when you take drugs which can make oral contraceptives less effective

HOW TO TAKE THE PILL

IMPORTANT POINTS TO REMEMBER

SEXUALLY TRANSMITTED DISEASES

This product (like all oral contraceptives) is intended to prevent pregnancy. It does not protect against transmission of HIV (AIDS) and other sexually transmitted diseases such as Chlamydia, genital herpes, genital warts, gonorrhea, hepatitis B, and syphilis.

BEFORE YOU START TAKING YOUR PILLS:

1. BE SURE TO READ THESE DIRECTIONS:

Before you start taking your pills.

Anytime you are not sure what to do.

2. THE RIGHT WAY TO TAKE THE PILL IS TO TAKE ONE PILL EVERY DAY AT THE SAME TIME.

If you miss pills you could get pregnant. This includes starting the pack late. The more pills you miss, the more likely you are to get pregnant.

3. MANY WOMEN HAVE SPOTTING OR LIGHT BLEEDING, OR MAY FEEL SICK TO THEIR STOMACH DURING THE FIRST 1-3 PACKS OF PILLS.

If you do feel sick to your stomach, do not stop taking the pill. The problem will usually go away. If it doesn’t go away, check with your doctor or clinic.

4. MISSING PILLS CAN ALSO CAUSE SPOTTING OR LIGHT BLEEDING, even when you make up these missed pills.

On the days you take 2 pills to make up for missed pills, you could also feel a little sick to your stomach.

5. IF YOU HAVE VOMITING OR DIARRHEA, for any reasons, or IF YOU TAKE SOME MEDICINES, including some antibiotics, your pills may not work as well.

Use a back-up method (such as condoms, foam or sponge) until you check with your doctor or clinic.

6. IF YOU HAVE TROUBLE REMEMBERING TO TAKE THE PILL, talk to your doctor or clinic about how to make pill-taking easier or about using another method of birth control.

7. IF YOU HAVE ANY QUESTIONS OR ARE UNSURE ABOUT THE INFORMATION IN THIS LEAFLET, call your doctor or clinic.

BEFORE YOU START TAKING YOUR PILLS

1. DECIDE WHAT TIME OF DAY YOU WANT TO TAKE YOUR PILL.

It is important to take it at about the same time every day.

2. LOOK AT YOUR PILL PACK TO SEE IF IT HAS 28 PILLS:

The 28 pill pack has 21 “active” light peach pills (with hormones) to take for 3 weeks, followed by 1 week of reminder white to off-white pills (without hormones).

Refer to the sample of the blister below.

* For use of day labels, see WHEN TO START THE FIRST PACK OF PILLS.

3. BE SURE YOU HAVE READY AT ALL TIMES:

ANOTHER KIND OF BIRTH CONTROL (such as condoms, foam or sponge) to use as a back-up in case you miss pills.

An EXTRA, FULL PILL PACK.

WHEN TO START THE FIRST PACK OF PILLS

You have a choice of which day to start taking your first pack of pills. BRIELLYN (norethindrone and ethinyl estradiol tablets USP) are available in the Blister Pack Tablet Dispenser which is designed for a Sunday Start. Day 1 Start is also provided. Decide with your doctor or clinic which is the best day for you. Pick a time of day which will be easy to remember. Pick the Days of the Week Sticker that starts with the first day of your period. When you have picked the right sticker, throw away the others and place the sticker on the blister over the pre-printed days of the week and make sure it lines up with the pills. If your Physician has instructed you to use a “Sunday Start” method, then use the blister which is set up for a Sunday start.

DAY-1 START:

1. Take the first “active” light peach pill of the first pack during the first 24 hours of your period.

2. You will not need to use a back-up method of birth control, since you are starting the pill at the beginning of your period.

SUNDAY START:

1. Take the first “active” light peach pill of the first pack on the Sunday after your period starts, even if you are still bleeding. If your period begins on Sunday, start the pack that same day.

2. Use another method of birth control as a back-up method if you have sex anytime from the Sunday you start your first pack until the next Sunday (7 days). Condoms, foam, or the sponge are good back-up methods of birth control.

WHAT TO DO DURING THE MONTH

1. TAKE ONE PILL AT THE SAME TIME EVERY DAY UNTIL THE PACK IS EMPTY.

Do not skip pills even if you are spotting or bleeding between monthly periods or feel sick to your stomach (nausea).

Do not skip pills even if you do not have sex very often.

2. WHEN YOU FINISH A PACK OR SWITCH YOUR BRAND OF PILLS:

28 pills: Start the next pack on the day after your last “reminder” pill. Do not wait any days between packs.

WHAT TO DO IF YOU MISS PILLS

If you MISS 1 light peach “active” pill:

1. Take it as soon as you remember. Take the next pill at your regular time. This means you may take 2 pills in 1 day.

2. You do not need to use a back-up birth control method if you have sex.

If you MISS 2 light peach “active” pills in a row in WEEK 1 OR WEEK 2 of your pack:

1. Take 2 pills on the day you remember and 2 pills the next day

2. Then take 1 pill a day until you finish the pack.

3.You MAY BECOME PREGNANT if you have sex in the 7 days after you miss pills

You MUST use another birth control method (such as condoms, foam or sponge) as a backup for those 7 days.

If you MISS 2 light peach “active” pills in a row in THE 3rd WEEK:

1. If you are a Day-1 Starter:

THROW OUT the rest of the pill pack and start a new pack that same day.

If you are a Sunday Starter:

Keep taking 1 pill every day until Sunday.

On Sunday, THROW OUT the rest of the pack and start a new pack of pills that same day.

2. You may not have your period this month but this is expected. However, if you miss your period 2 months in a row, call your doctor or clinic because you might be pregnant.

3. You MAY BECOME PREGNANT if you have sex in the 7 days after you miss pills. You MUST use another birth control method (such as condoms, foam or sponge) as a back-up for those 7 days.

If you MISS 3 OR MORE light peach “active” pills in a row (during the first 3 weeks):

1. If you are a Day-1 Starter:

THROW OUT the rest of the pill pack and start a new pack that same day.

If you are a Sunday Starter:

Keep taking 1 pill every day until Sunday.

On Sunday, THROW OUT the rest of the pack and start a new pack of pills that same day.

2. You may not have your period this month but this is expected. However, if you miss your period 2 months in a row, call your doctor or clinic because you might be pregnant.

3. You MAY BECOME PREGNANT if you have sex in the 7 days after you miss pills. You MUST use another birth control method (such as condoms, foam or sponge) as a back-up for those 7 days

A REMINDER FOR THOSE ON 28-DAY PACKS:

If you forget any of the 7 white to off-white “reminder” pills in Week 4:

THROW AWAY the pills you missed.

Keep taking 1 pill each day until the pack is empty. You do not need a back-up method

FINALLY, IF YOU ARE STILL NOT SURE WHAT TO DO ABOUT THE PILLS YOU HAVE MISSED:

Use a BACK-UP METHOD anytime you have sex.

KEEP TAKING ONE “ACTIVE” PILL EACH DAY until you can reach your doctor or clinic.

GENERAL:

1. Pregnancy Due to Pill Failure:

The incidence of pill failure resulting in pregnancy is approximately 1% (i.e., one pregnancy per 100 women per year) if taken every day as directed, but more typical failure rates are about 3%. If failure does occur, the risk to the fetus is minimal.

2. Pregnancy After Stopping the Pill:

There may be some delay in becoming pregnant after you stop using oral contraceptives, especially if you had irregular menstrual cycles before you used oral contraceptives. It may be advisable to postpone conception until you begin menstruating regularly once you have stopped taking the pill and desire pregnancy.

There does not appear to be any increase in birth defects in newborn babies when pregnancy occurs soon after stopping the pill.

3. Other:

a. Overdosage:

Serious ill effects have not been reported following ingestion of large doses of oral contraceptives by young children. Overdosage may cause nausea and withdrawal bleeding in females. In case of overdosage, contact your poison control center, health care professional, or nearest emergency room. KEEP THIS DRUG AND ALL DRUGS OUT OF THE REACH OF CHILDREN.

b. General Medical Information:

Your health care professional will take a medical and family history before prescribing oral contraceptives and examine you. The physical examination may be delayed to another time if you request it and the health care provider believes that it is a good medical practice to postpone it. You should be reexamined at least once per year. Be sure to inform your health care professional if there is a family history of any of the conditions listed previously in this leaflet. Be sure to keep all appointments with your health care professional, because this is a time to determine if there are early signs of side effects of oral contraceptive use.

Do not use the drug for any condition other than the one for which it was prescribed. This drug has been prescribed specifically for you; do not give it to others who may want birth control pills

NONCONTRACEPTIVE EFFECTS OF ORAL CONTRACEPTIVES:

In addition to preventing pregnancy, use of oral contraceptives may provide certain benefits. They are:

- Menstrual cycles may become more regular
- Blood flow during menstruation may be lighter and less iron may be lost. Therefore, anemia due to iron deficiency is less likely to occur
- Pain or other symptoms during menstruation may be encountered less frequently
- Ectopic (tubal) pregnancy may occur less frequently
- Non-cancerous cysts or lumps in the breast may occur less frequently
- Acute pelvic inflammatory disease may occur less frequently
- Oral contraceptive use may provide some protection against developing two forms of cancer: cancer of the ovaries and cancer of the lining of the uterus.

If you want more information about birth control pills, ask your doctor or pharmacist. They have a more technical leaflet called the Professional Labeling, which you may wish to read.

Distributed by:

Glenmark Pharmaceuticals Inc., USA

Elmwood Park, NJ 07407

Questions? 1 (888) 721-7115

www.glenmarkpharma-us.com

May 2025